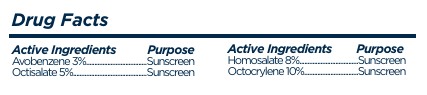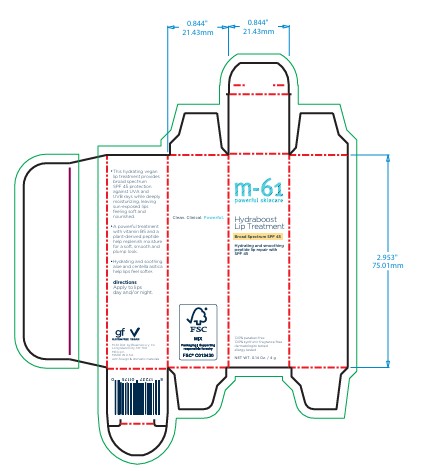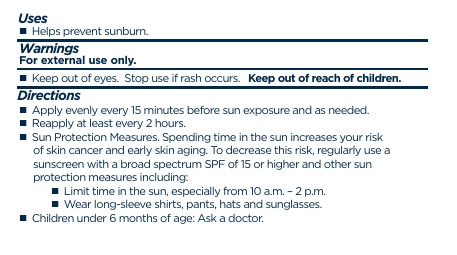 DRUG LABEL: Hydraboost Lip Treatment
NDC: 72203-021 | Form: STICK
Manufacturer: Bluemercury
Category: otc | Type: HUMAN OTC DRUG LABEL
Date: 20251209

ACTIVE INGREDIENTS: AVOBENZONE 3 g/100 g; HOMOSALATE 8 g/100 g; OCTOCRYLENE 10 g/100 g; OCTISALATE 5 g/100 g
INACTIVE INGREDIENTS: .BETA.-SITOSTEROL; HYDROGENATED OLIVE OIL; CALENDULA OFFICINALIS SEED OIL; SAMBUCUS NIGRA FRUIT JUICE; ALPHA-TOCOPHEROL ACETATE; LACTIC ACID; PANTHENOL; POLYETHYLENE; HELIANTHUS ANNUUS (SUNFLOWER) SEED OIL; CENTELLA ASIATICA; LIMONENE, (-)-; CARICA PAPAYA (PAPAYA) FRUIT JUICE; HYDROGENATED SOYBEAN OIL; HYDROGENATED JOJOBA OIL; PEG-10 .BETA.-SITOSTEROL; SORBITAN SESQUIOLEATE; MICROCRYSTALLINE WAX; BUTYLOCTYL SALICYLATE; GLYCYRRHIZA GLABRA (LICORICE) ROOT; PHENOXYETHANOL; GLYCOLIC ACID; PALMITOYL HEXAPEPTIDE-12; MORUS ALBA LEAF; CITRIC ACID; BIS-DIGLYCERYL POLYACYLADIPATE-2; C12-15 ALKYL BENZOATE; MENTHA PIPERITA (PEPPERMINT) OIL; TRIBEHENIN; TETRAHEXYLDECYL ASCORBATE; LINALOOL; GLYCERIN; GLYCINE SOJA (SOYBEAN) STEROLS; CERAMIDE NG; TOCOPHEROL; TAMARINDUS INDICA SEED; WATER; SODIUM HYALURONATE; PENTYLENE GLYCOL; ALOE BARBADENSIS LEAF JUICE

Hydraboost Lip Treatment

Drug Facts

ACTIVE INGREDIENT

Avobenzene 3%

Octisalate 5%

Homosalate 8%

Octocrylene 10%

Uses

- Helps prevent sunburn.

Warnings

For external use only.

DO NOT USE

Keep out of eyes.

Stop use if rash occurs.

Keep out of reach of children.

Inactive Ingredients

Hydrogenated Soybean Oil, Hydrogenated Olive Oil, Microcrystalline Wax, Bis-Diglyceryl, Polyacyladipate-2, Hydrogenated Jojoba Oil, Butyloctyl Salicylate, Polyethylene, Glycine Soja (Soybean) Lipids, C12-15 Alkyl Benzoate, Sorbitan Sesquioleate, Palmitoyl Hexapeptide-12, Panthenol, Aloe Barbadensis Leaf Extract, Sodium Hyaluronate, Centella Asiatica Extract, Tamarindus Indica Seed Gum, Glycolic Acid, Tocopherol, Calendula Officinalis Extract , Mentha Piperita (Peppermint) Oil, Helianthus Annuss (Sunflower) Seed Oil, Glycyrrhiza Glabra (Licorice) Root Extract, Carica Papaya (Papaya) Fruit Extract, Sambucus Nigra Fruit Extract, Morus Alba Leaf Extract, Water, Tribehenin, Ceramide Ng, Phytosterols, Peg-10 Phytosterol, Tetrahexyldecyl Ascorbate, Glycerin, Pentylene Glycol.

Other Information

Protect the product in this continer from excessive heat and direct sun

Questions?

800-914-6000 Monday-Sunday 9am-9pm EST

Principal Display Panel - 4 g Tube Carton

m-61

powerful skincare

Hydraboost

Lip Treatment

Broad Spectrum SPF 45

Hydrating and smoothing peptide lip repair with SPF 45

100% paraben-free

100% synthetic fragrance-free

dermatologist tested

allergy tested

NET WT. 0.14 Oz / 4 g